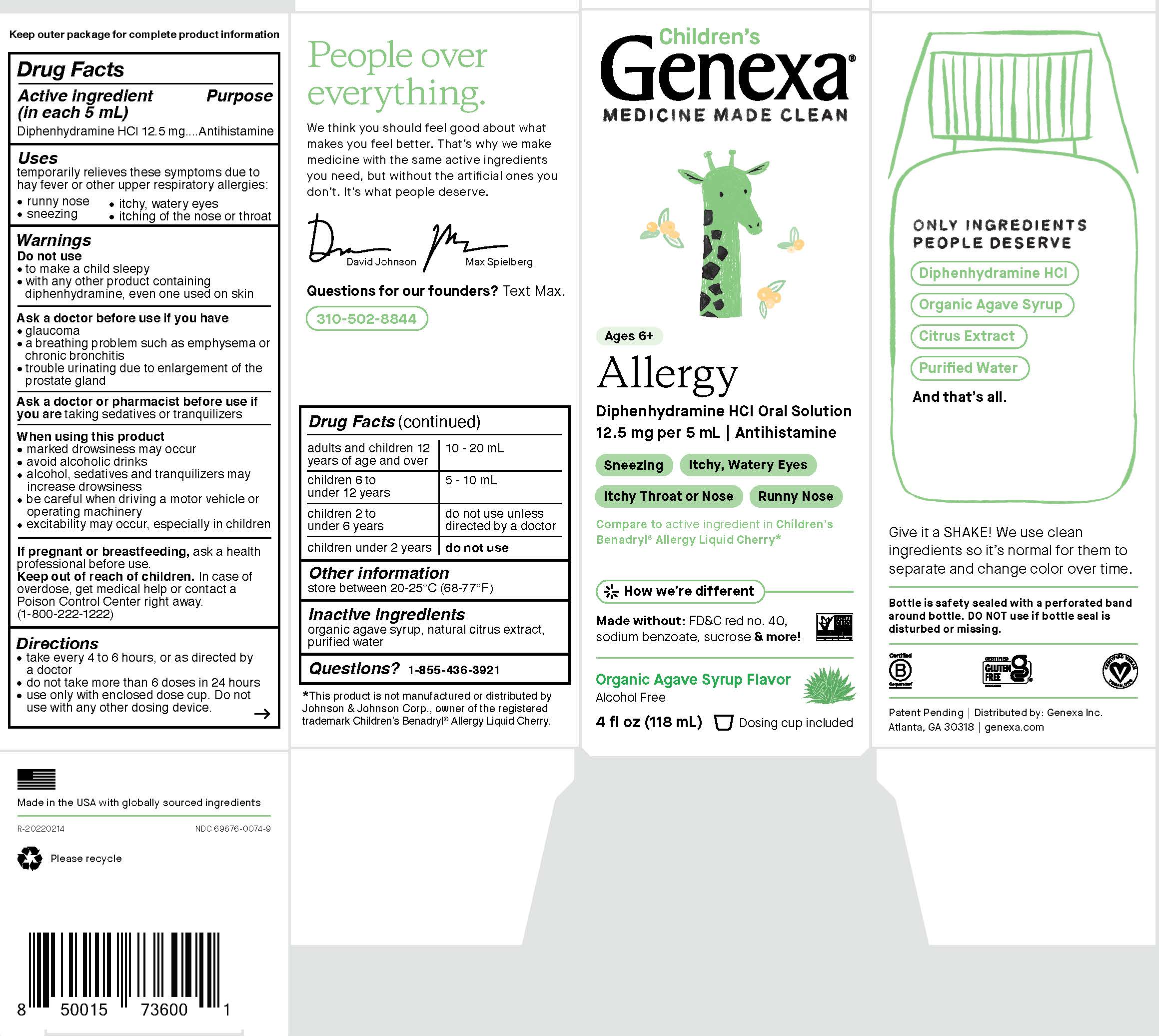 DRUG LABEL: Childrens Allergy
NDC: 69676-0074 | Form: SOLUTION
Manufacturer: Genexa Inc.
Category: otc | Type: HUMAN OTC DRUG LABEL
Date: 20250220

ACTIVE INGREDIENTS: DIPHENHYDRAMINE HYDROCHLORIDE 12.5 mg/5 mL
INACTIVE INGREDIENTS: AGAVE TEQUILANA JUICE; WATER; CITRUS FRUIT

Children's Allergy

Drug Facts

Active ingredient (in each 5 mL)

Diphenhydramine HCl 12.5 mg

Purpose

Antihistamine

Uses

temporarily relieves these symptoms due to hay fever or other upper respiratory allergies:

- runny nose
- sneezing
- itchy, watery eyes
- itching of the nose or throat

Warnings

Do not use

- to make a child sleepy
- with any other product containing diphenhydramine, even one used on skin

Ask a doctor before use if you have

- glaucoma
- a breathing problem such as emphysema or chronic bronchitis
- trouble urinating due to enlargement of the prostate gland

Ask a doctor or pharmacist before use if you are taking sedatives or tranquilizers

When using this product

- marked drowsiness may occur
- avoid alcoholic drinks
- alcohol, sedatives and tranquilizers may increase drowsiness
- be careful when driving a motor vehicle or operating machinery
- excitability may occur, especially in children

PREGNANCY OR BREAST FEEDING

If pregnant or breastfeeding, ask a health professional before use.

Keep out of reach of children. In case of overdose, get medical help or contact a Poison Control Center right away. (1-800-222-1222)

Directions

- take every 4 to 6 hours, or as directed by a doctor
- do not take more than 6 doses in 24 hours
- use only with enclosed dose cup. Do not use with any other dosing device.

adults and children 12 years of age and over | 10 - 20 mL
children 6 to under 12 years | 5 - 10 mL
children 2 to under 6 years | do not use unless directed by a doctor
children under 2 years | do not use

Other information

store between 20-25°C (68-77°F)

Inactive ingredients

organic agave syrup, natural citric extract, purified water

Questions?

1-855-436-3921

*This product is not manufactured or distributed by

Johnson & Johnson Corp., owner of the registered

trademark Children's Benadryl® Allergy Liquid Cherry.

Bottle is safety sealed with a perforated band around bottle.

DO NOT use if bottle seal is disturbed or missing.

Patent Pending | Distributed by: Genexa Inc.

Atlanta, GA 30318 | genexa.com

Made in the USA with globally sourced ingredients.

NDC 69676-0074-9

Directions

take every 4 to 6 hours, or as directed by a doctor
do not take more than 6 doses in 24 hours
use only with enclosed dose cup. Do not use with any other dosing device.

adults and children 12 years of age and over | 10 - 20 mL
children 6 to under 12 years | 5 - 10 mL
children 2 to under 6 years | do not use unless directed by a doctor
children under 2 years | do not use

PACKAGE LABEL

Children's

Genexa®

MEDICINE MADE CLEAN

Ages 6+

Allergy

Diphenhydramine HCl Oral Solution

12.5 mg per 5 mL | Antihistamine

Sneezing

Itchy, Watery Eyes

Itchy Throat or Nose

Runny Nose

Compareto active ingredient in Children’s
Benadryl® Allergy Liquid Cherry*

How we're different

Made without:

FD&C red no. 40,

sodium benzoate, sucrose & more!

Organic Agave Syrup Flavor

Alcohol Free

4 FL OZ (118 mL) Dosing cup included